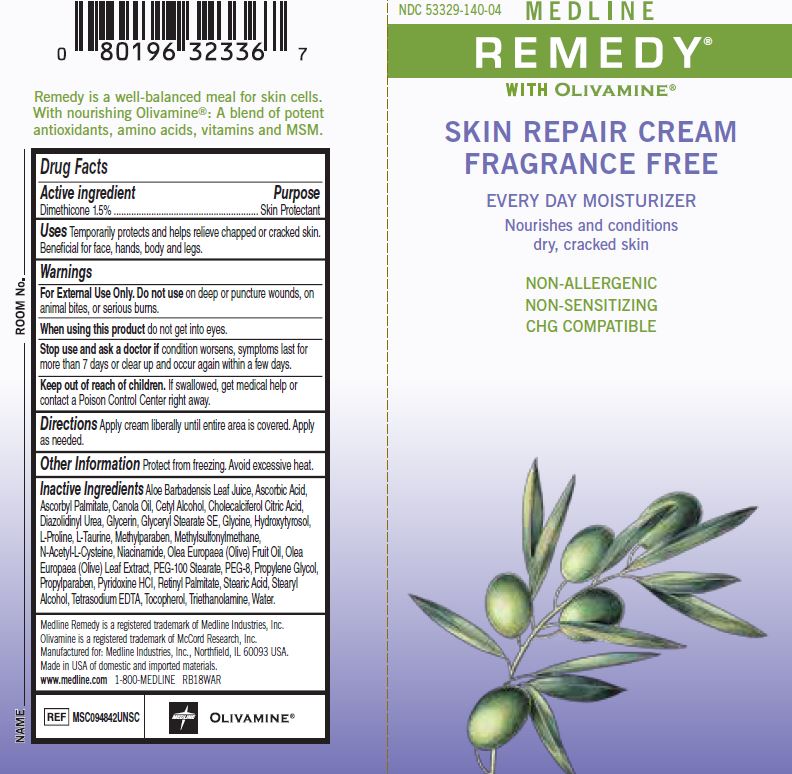 DRUG LABEL: Remedy Skin Repair
NDC: 53329-140 | Form: CREAM
Manufacturer: Medline Industries, LP
Category: otc | Type: HUMAN OTC DRUG LABEL
Date: 20251028

ACTIVE INGREDIENTS: DIMETHICONE 1.5 g/100 mL
INACTIVE INGREDIENTS: ALOE VERA LEAF; ASCORBIC ACID; ASCORBYL PALMITATE; CANOLA OIL; CETYL ALCOHOL; CHOLECALCIFEROL; CITRIC ACID MONOHYDRATE; DIAZOLIDINYL UREA; GLYCERIN; GLYCERYL MONOSTEARATE; GLYCINE; PROLINE; TAURINE; METHYLPARABEN; DIMETHYL SULFONE; ACETYLCYSTEINE; NIACINAMIDE; OLIVE OIL; POLYETHYLENE GLYCOL 400; PEG-100 STEARATE; PROPYLENE GLYCOL; PROPYLPARABEN; PYRIDOXINE HYDROCHLORIDE; VITAMIN A PALMITATE; STEARIC ACID; STEARYL ALCOHOL; EDETATE SODIUM; .ALPHA.-TOCOPHEROL; TROLAMINE; WATER

140 Remedy Olivamine Skin Repair Cream (unscented)

Active ingredient

Dimethicone 1.5%

Purpose

Skin Protectant

Uses

temporarily protects and helps relieve chapped or cracked skin. Beneficial for face, hands, body and legs.

Warnings

For External Use Only.

Do not use

on deep or puncture wounds, on animal bites, or serious burns

When using this product

do not get into eyes.

Stop use and ask a doctor if

condition worsens, symptoms last for more than 7 days or clear up and occur again within a few days.

Keep out of reach of children.

If swallowed, get medical help or contact a Poison Control Center right away.

Directions

- apply cream liberally until entire area is covered
- apply as needed

Other information

- protect from freezing, avoid excessive heat

Inactive ingredients

aloe barbadensis leaf juice, ascorbic acid, ascorbyl palmitate, canola oil, cetyl alcohol, cholecalciferol citric acid, diazolidinyl urea, glycerin, glyceryl stearate SE, glycine, hydroxytyrosol, L-proline, L-taurine, methylparaben, methylsulfonylmethane, A-acetyl-L-cysteine, niacinamide, olea europaea (olive) fruit oil, olea europaea (olive) leaf extract, PEG-100 stearate, PEG-8, propylene glycol, propylparaben, pyridoxine HCl, retinyl palmitate, stearic acid, stearyl alcohol, tetrasodium EDTA, tocopherol, triethanolamine, water

Manufacturing Information

Medline Remedy is a registered trademark of Medline Industries, Inc.

Olivamine is a registered trademark of McCord Research, Inc.

Manufactured for: Medline Industries, LP,

Three Lakes Drive, Northfield, IL 60093 USA

Made in USA of domestic and imported materials

www.medline.com

1-800-MEDLINE

REF: MSC094842UNSC